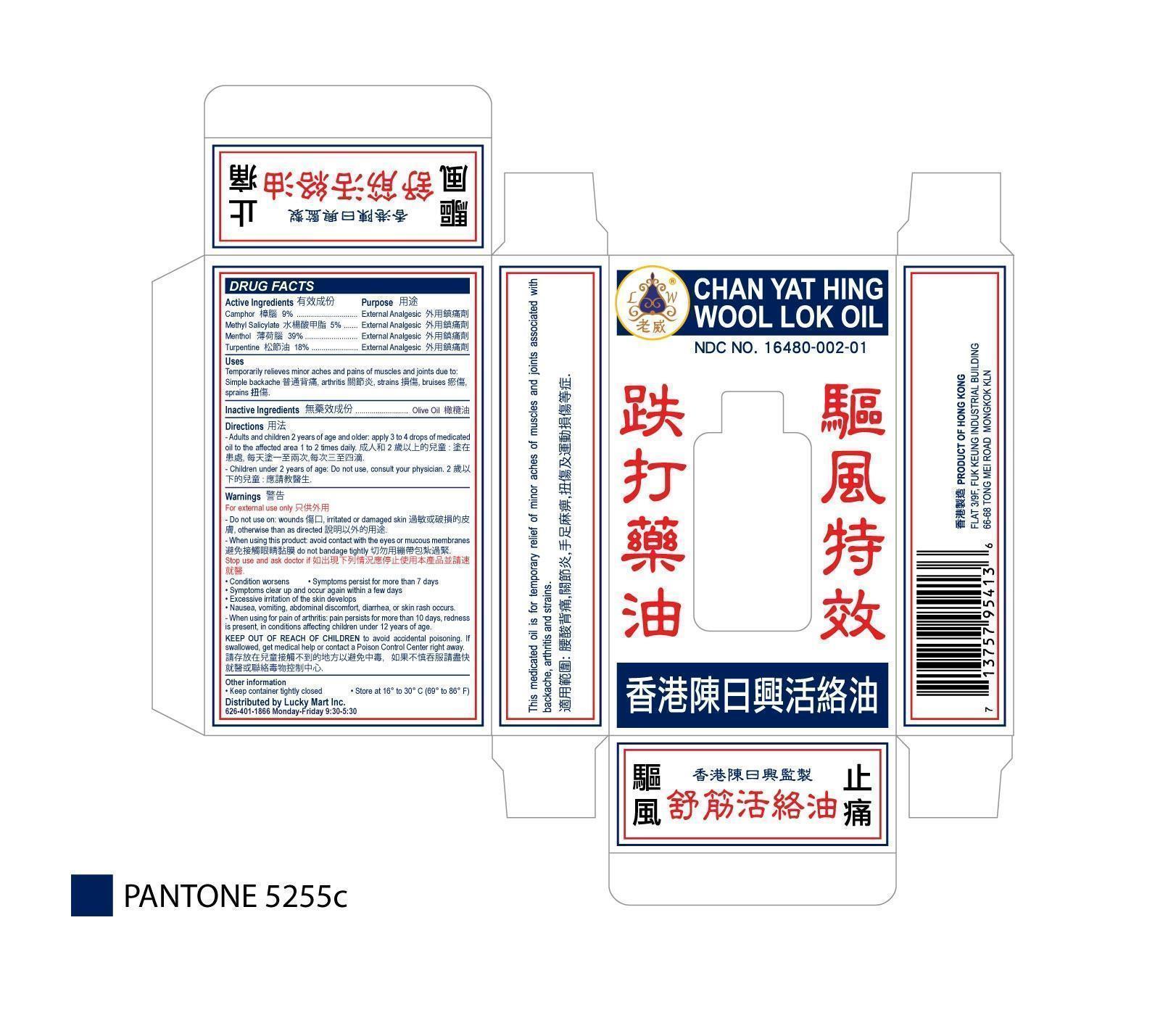 DRUG LABEL: Chan Yat Hing She Kun Wool Lok Medicated Oil
NDC: 16480-002 | Form: OIL
Manufacturer: Chan Yat Hing Medicine Factory
Category: otc | Type: HUMAN OTC DRUG LABEL
Date: 20131209

ACTIVE INGREDIENTS: CAMPHOR (SYNTHETIC) 9 g/100 mL; METHYL SALICYLATE 5 g/100 mL; MENTHOL 39 g/100 mL; TURPENTINE OIL 18 g/100 mL
INACTIVE INGREDIENTS: OLIVE OIL

CHAT YAT HING SHE KUN WOOL LOK MEDICATED OIL

Active Ingredients

Camphor 9%

Methyl Salicylate 5%

Menthol 39%

Turpentine 18%

Purpose

Camphor External Analgesic

Methyl Salicylate External Analgesic

Menthol External Analgesic

Turpentine External Analgesic

Uses

Temporarily relieves minor aches and pains of muscles and joints due to: simple backaches, arthritis, strains, bruises, sprains

DIRECTIONS

Adults and children 2 years of age and older: apply 3 to 4 drops of medicated oil to the affected area 1 to 2 times daily. Children under 2 years of age: Do not use, consult your physician.

Warnings

For external use only. Do not use on wounds, irritated or damaged skin, otherwise than as directed. When using this product, avoid contact with the eyes or mucous membranes. Do not bandage tightly.

Warnings

Keep out of reach of children to avoid accidental poinsoning. If swallowed, get medical help or contact a Poison Center right away.

Warnings

Stop use and ask doctor if

Condition worsens

Symptoms persist for more than 7 days

Symptoms clear up and occur again within a few days

Excessive irritation of the skin develops

Nausea, vomitting, abdominal discomfort, diarrhea, or skin rash occurs

When using for pain of arthritis: pain persits for more than 10 days, redness is present, in conditions affecting children 12 years of age.

Directions

Apply 3 to 4 drops of medicated oil to the affected area 1 to 2 times daily.

Other Information

Keep container tightly closed. Store at 16 to 30 degrees centigrade (69 to 86 Farenheit).

Inactive Ingredients

Olive Oil